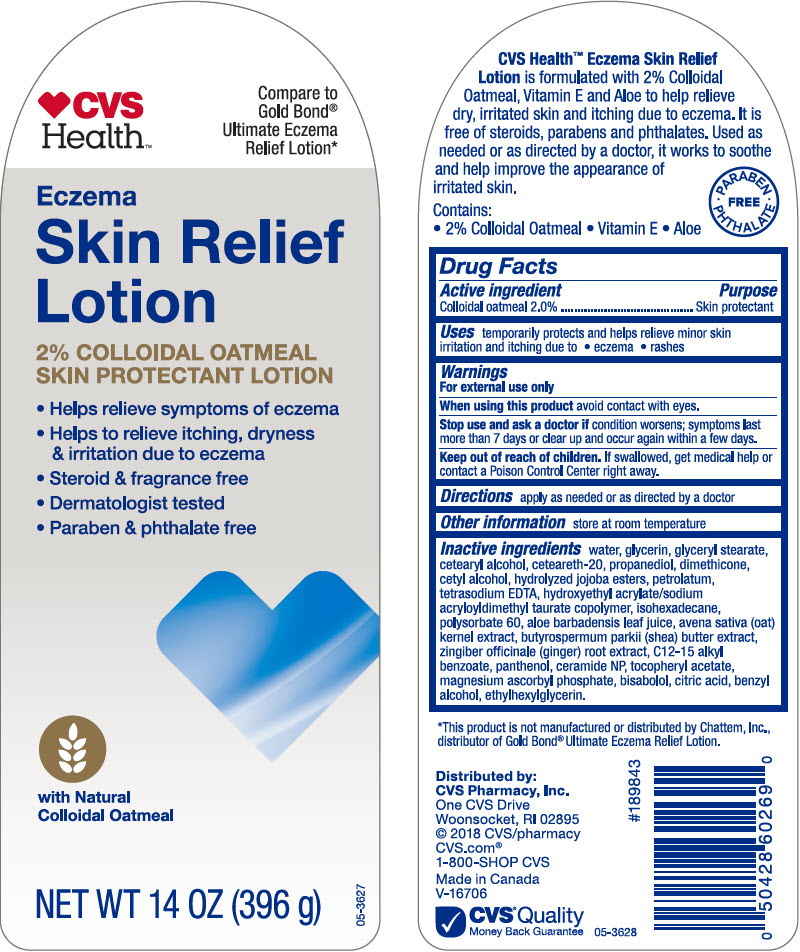 DRUG LABEL: CVS Health Eczema Skin Relief 
NDC: 69842-962 | Form: LOTION
Manufacturer: CVS Health
Category: otc | Type: HUMAN OTC DRUG LABEL
Date: 20200129

ACTIVE INGREDIENTS: Oatmeal 20 mg/1 g
INACTIVE INGREDIENTS: Water; Glycerin; Glyceryl Monostearate; Cetostearyl Alcohol; Polyoxyl 20 Cetostearyl Ether; Propanediol; Dimethicone; Cetyl Alcohol; Hydrolyzed Jojoba Esters (Acid Form); Petrolatum; Edetate Sodium; HYDROXYETHYL ACRYLATE/SODIUM ACRYLOYLDIMETHYL TAURATE COPOLYMER (100000 MPA.S AT 1.5%); Isohexadecane; Polysorbate 60; Aloe Vera Leaf; Oat; Shea Butter; Ginger; Alkyl (C12-15) Benzoate; Panthenol; Ceramide NP; .ALPHA.-TOCOPHEROL ACETATE, DL-; Magnesium Ascorbyl Phosphate; Levomenol; Citric Acid Monohydrate; BENZYL ALCOHOL; ETHYLHEXYLGLYCERIN

CVS Health™ Eczema Skin Relief Lotion
Skin Protectant

Drug Facts

Active ingredients

Colloidal oatmeal 2.0%

Purpose

Skin protectant

Uses

temporarily protects and helps relieve minor skin irritation and itching due to

⬥ eczema
⬥ rashes

Warnings

For external use only

When using this product avoid contact with eyes.

Stop use and ask a doctor if condition worsens; symptoms last more than 7 days or clear up and occur again within a few days.

Keep out of reach of children. If swallowed, get medical help or contact a Poison Control Center right away.

Directions

apply as needed or as directed by a doctor

Other information

store at room temperature

Inactive ingredients

water, glycerin, glyceryl stearate, cetearyl alcohol, ceteareth-20, propanediol, dimethicone, cetyl alcohol, hydrolyzed jojoba esters, petrolatum, tetrasodiun EDTA, hydroxyethyl acrylate/sodium acryloyldimethyl taurate copolymer, isohexadecane, polysorbate 60, aloe barbadensis leaf juice, avena sativa (oat) kernel extract, butyrospermum parkii (shea) butter extract, zingiber officinale (ginger) root extract, C12-15 alkyl benzoate, panthenol, ceramide NP, tocopheryl acetate, magnesium ascorbyl phosphate, bisabolol, citric acid, benzyl alcohol, ethylhexylglycerin.

Distributed by:
CVS Pharmacy, Inc.
One CVS Drive
Woonsocket, RI 02895

PRINCIPAL DISPLAY PANEL - 396 g Bottle Label

CVS
Health™

Compare to
Gold Bond®
Ultimate Eczema
Relief Lotion*

Eczema
Skin Relief
Lotion

2% COLLOIDAL OATMEAL
SKIN PROTECTANT LOTION

- Helps relieve symptoms of eczema
- Helps to relieve itching, dryness
  & irritation due to eczema
- Steroid & fragrance free
- Dermatologist tested
- Paraben & phthalate free

with Natural
Colloidal Oatmeal

NET WT 14 OZ (396 g)

05-3627